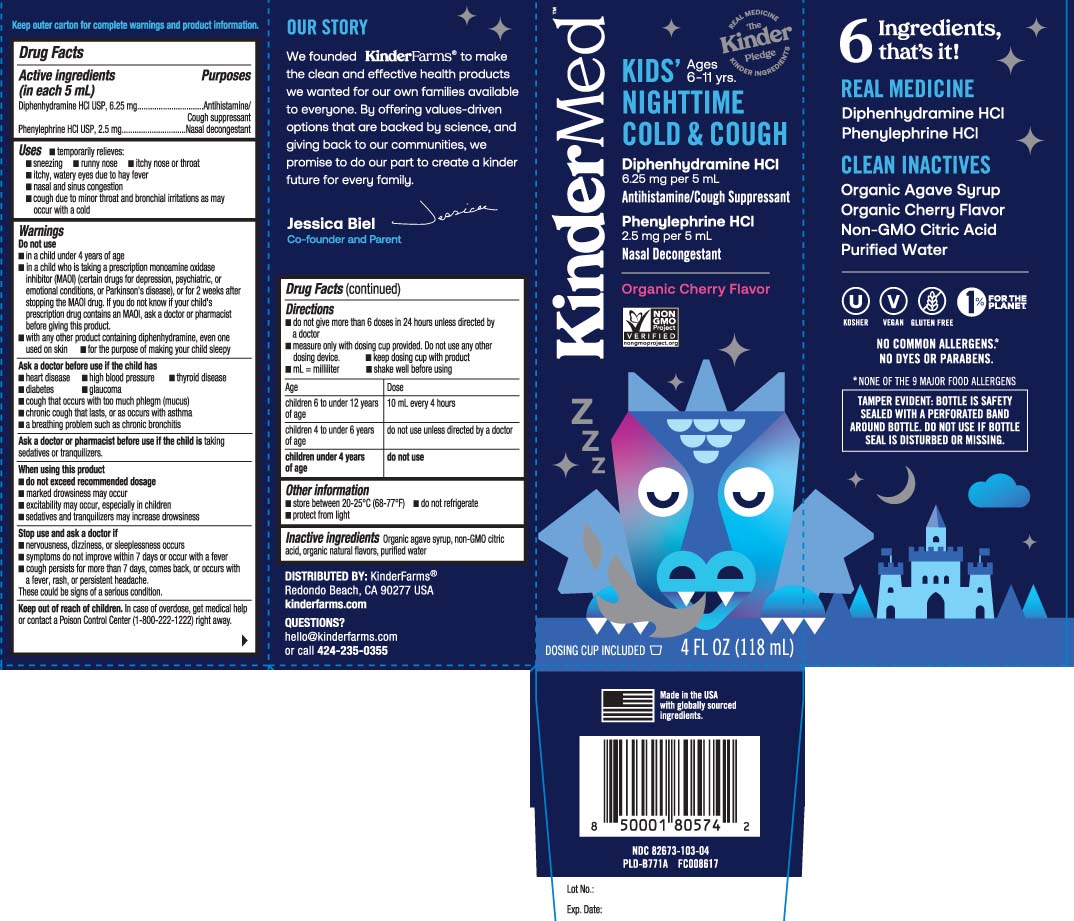 DRUG LABEL: Childrens Nighttime Cold and Cough
NDC: 82673-103 | Form: LIQUID
Manufacturer: KinderFarms, LLC
Category: otc | Type: HUMAN OTC DRUG LABEL
Date: 20240410

ACTIVE INGREDIENTS: DIPHENHYDRAMINE HYDROCHLORIDE 6.25 mg/5 mL; PHENYLEPHRINE HYDROCHLORIDE 2.5 mg/5 mL
INACTIVE INGREDIENTS: AGAVE TEQUILANA JUICE; CITRIC ACID MONOHYDRATE; WATER

Drug Facts

Active ingredients (in each 5 mL)

Diphenhydramine HCl 6.25 mg

Phenylephrine HCl 2.5 mg

Purposes

Antihistamine/

Cough suppressant

Nasal decongestant

Uses

temporarily relieves:

- sneezing
- runny nose
- itchy nose or throat
- itchy, watery eyes due to hay fever
- nasal and sinus congestion
- cough due to minor throat and bronchial irritation as may occur with a cold

Warnings

Do not use

- in a child under 4 years of age
- in a child who is taking a prescription monoamine oxidase inhibitor (MAOI) (certain drugs for depression, psychiatric or emotional conditions, or Parkinson's disease), or for 2 weeks after stopping the MAOI drug contains an MAOI, ask a doctor or pharmacist before giving this product.
- with any other product containing diphenhydramine, even one used on skin
- for the purpose of making your child sleepy

Ask a doctor before use if the chld has

- heart disease
- high blood pressure
- thyroid disease
- diabetes
- glaucoma
- cough that occurs with too much phlegm (mucus)
- chronic cough that lasts, or as occurs with asthma
- a breathing problem such as chronic bronchitis

Ask a doctor or pharmacist before use if the child is

taking sedatives or tranquilizers

When using this product

- do not exceed recommended dosage
- marked drowsiness may occur
- excitability may occur, especially in children
- sedatives and tranquilizers may increase drowsiness

Stop use and ask a doctor if

- nervousness, dizziness or sleeplessness occur
- symptoms do not improve within 7 days or occur with a fever
- cough persists for more than 7 days, comes back or occurs with a fever, rash or persistent headache.

These could be signs of a serious condition.

Keep out of reach of children.

In case of overdose, get medical help or contact a Poison Control Center (1-800-222-1222) right away.

Directions

- do not give more than 6 doses in any 24-hours unless directed by a doctor
- measure only with dosing cup provided. Do not use any other dosing device
- keep dosing cup with product
- mL= milliliter
- shake well before using

age | dose
children 6 to under12 years of age | 10 mL every 4 hours
children 4 to under 6 years of age | do not use unless directed by a doctor
children under 4 years of age | do not use

Other information

- store between 20-25º (68-77ºF)
- do not refrigerate
- protect from light

Inactive ingredients

Organic agave syrup, non-GMO citric acid, organic natural flavors, purified water

QUESTIONS?

Call 424-235-0355

Principal Display Panel

KIDS NIGHTTIME COLD & COUGH Age 6-11 yrs

Diphenhydramine HCl 6.25 mg per 5 mL

Antihistamine/ Cough Suppressant

Phenylephrine HCl 2.5 mg per 5 mL

Nasal Decongestant

Organic Cherry Flavor

NO COMMON ALLERGENS.

NO DYES OR PARABENS.

DOSING CUP INCLUDED

FL OZ (mL)

TAMPER EVIDENT: BOTTLE IS SAFETY SEALED. SEALED WITH A PERFORATED BAND AROUND BOTTLE. DO NOT USE IF BOTTLE SEAL IS DISTURBED OR MISSING.

Keep outer carton for complete warnings and product information.

DISTRIBUTED BY: KinderFarms®

Redondo Beach, CA 90277 USA

kinderfarms.com

Package Label

KINDERMED Kids Nighttime Cold & Cough Cherry Flavor